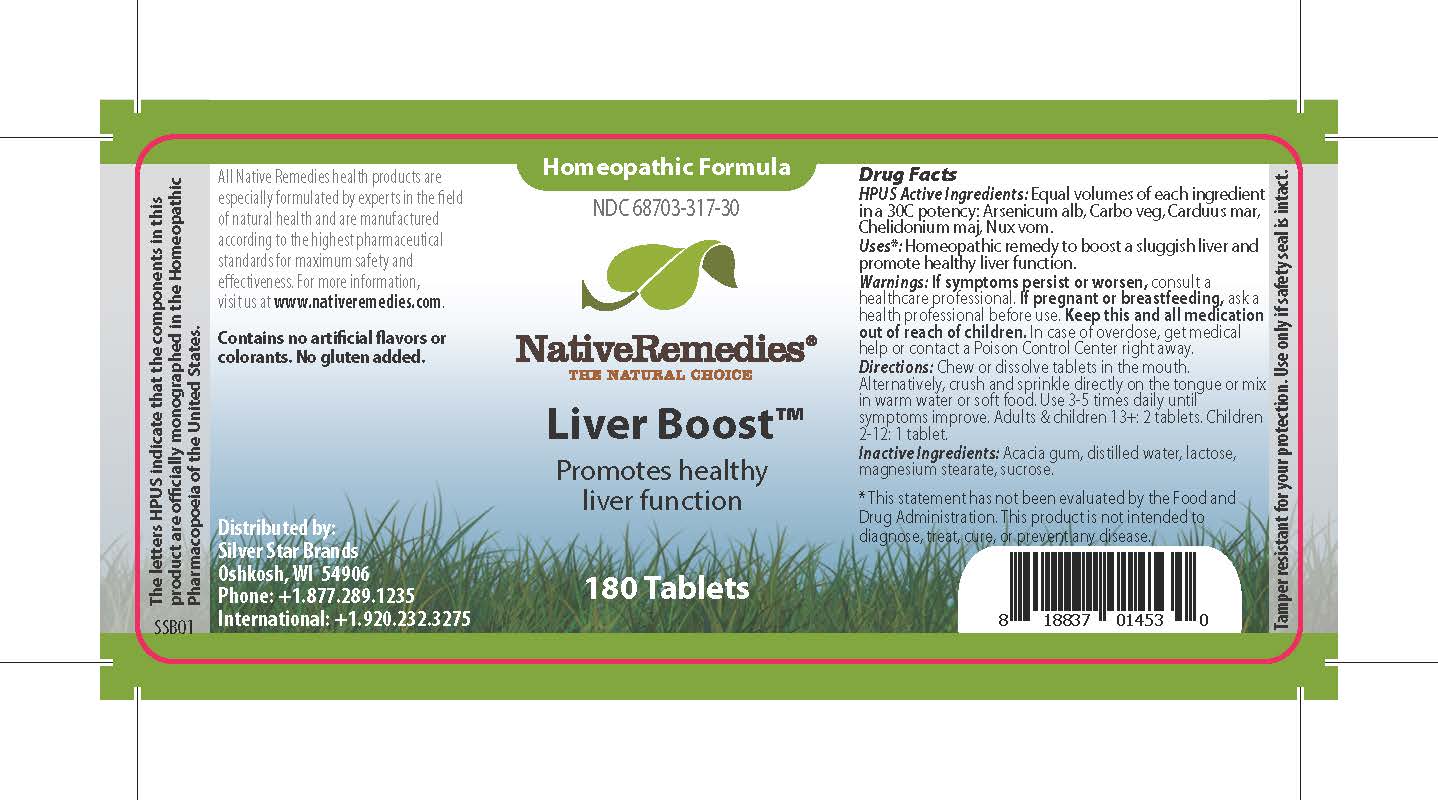 DRUG LABEL: Liver Boost
NDC: 68703-317 | Form: TABLET
Manufacturer: Silver Star Brands
Category: homeopathic | Type: HUMAN OTC DRUG LABEL
Date: 20241203

ACTIVE INGREDIENTS: SILYBUM MARIANUM SEED 30 [hp_C]/1 1; ARSENIC TRIOXIDE 30 [hp_C]/1 1; ACTIVATED CHARCOAL 30 [hp_C]/1 1; CHELIDONIUM MAJUS 30 [hp_C]/1 1; STRYCHNOS NUX-VOMICA SEED 30 [hp_C]/1 1
INACTIVE INGREDIENTS: MAGNESIUM STEARATE; LACTOSE, UNSPECIFIED FORM; ACACIA; SUCROSE; WATER

NativeRemedies® Liver Boost™

HPUS Active Ingredients: Equal volumes of each ingredient in a 30C potency: Arsenicum alb, Carbo veg, Carduus mar, Chelidonium maj, Nux vom.

The letters HPUS indicate that the components in this product are officially monographed in the Homeopathic pharmacopoeia of the United States.

Uses*

Uses*: Homeopathic remedy to boost a sluggish liver and promote healthy liver function.

*This statement has not been evaluated by the Food and Drug Administration. This product is not intended to diagnose, treat, cure, or prevent any disease.

Warnings

Warnings: If symptoms persist or worsen, consult a healthcare professional. If pregnant or breastfeeeding, ask a health professional before use. Keep this and all medication out of reach of children. In case of overdose, get medical help or contact a Poison Control Center right away.

Directions

Directions: Chew or dissolve tablets in the mouth. Alternatively, crush and sprinkle directly on the tongue or mix in warm water or soft food. Adults & children 13+: 2 tablets. Children 2-12: 1 tablet.

OTHER SAFETY INFORMATION

Contains no artificial flavors or colorants. No gluten added.

Tamper resistant for your protection. Use only if safety seal is intact.

Inactive Ingredients

Inactive Ingredients: Acacia gum, distilled water, lactose, magnesium stearate, sucrose.

KEEP OUT OF REACH OF CHILDREN

Keep this an all medication out of reach of children.

PREGNANCY OR BREAST FEEDING

If pregnant or breastfeeding, ask a health professional before use.

PURPOSE

Promotes healthy liver function